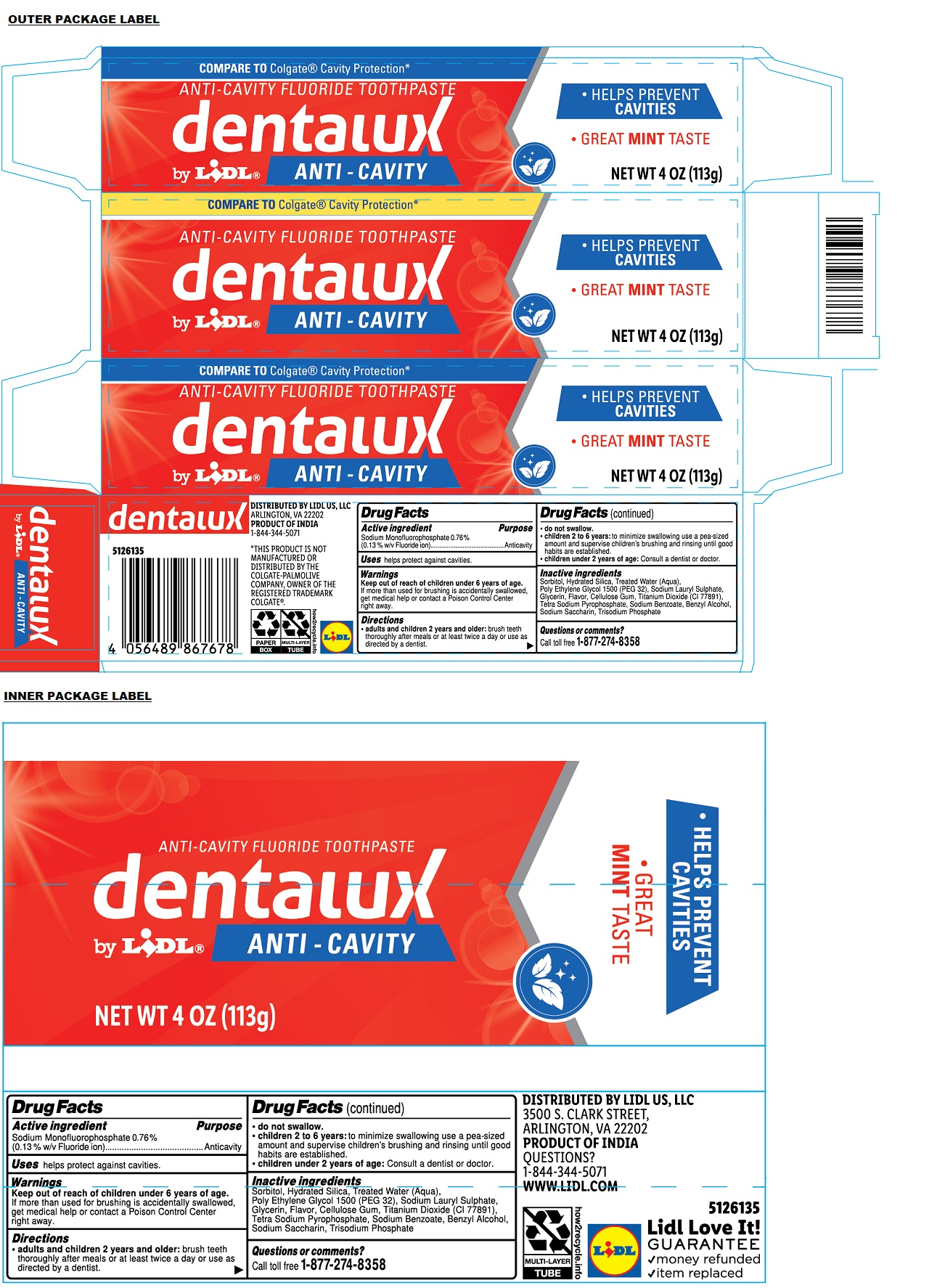 DRUG LABEL: dentalux ANTI-CAVITY FLUORIDE
NDC: 71141-186 | Form: PASTE, DENTIFRICE
Manufacturer: Lidl US, LLC
Category: otc | Type: HUMAN OTC DRUG LABEL
Date: 20240702

ACTIVE INGREDIENTS: SODIUM MONOFLUOROPHOSPHATE 0.13 g/100 g
INACTIVE INGREDIENTS: SORBITOL; HYDRATED SILICA; WATER; POLYETHYLENE GLYCOL 1600; SODIUM LAURYL SULFATE; GLYCERIN; CARBOXYMETHYLCELLULOSE SODIUM, UNSPECIFIED; TITANIUM DIOXIDE; SODIUM PYROPHOSPHATE; SODIUM BENZOATE; BENZYL ALCOHOL; SACCHARIN SODIUM; SODIUM PHOSPHATE, TRIBASIC, ANHYDROUS

dentalux ANTI-CAVITY FLUORIDE TOOTHPASTE

Active ingredient

Sodium Monofluorophosphate 0.76%
(0.13% w/v Fluoride ion)

Purpose

Anticavity

Uses

helps protect against cavities.

Warnings

Keep out of reach of children under 6 years of age. If more than used for brushing is accidentally swallowed, get medical help or contact a Poison Control Center right away.

Directions

• adults and children 2 years and older: brush teeth thoroughly after meals or at least twice a day or use as directed by a dentist.
• do not swallow.
• children 2 to 6 years: to minimize swallowing use a pea-sized amount and supervise children's brushing and rinsing until good habits are established.
• children under 2 years of age: Consult a dentist or doctor.

Inactive ingredients

Sorbitol, Hydrated Silica, Treated Water (Aqua), Poly Ethylene Glycol 1500 (PEG 32), Sodium Lauryl Sulphate, Glycerin, Flavor, Cellulose Gum, Titanium Dioxide (CI 77891), Tetra Sodium Pyrophosphate, Sodium Benzoate, Benzyl Alcohol, Sodium Saccharin, Trisodium Phosphate

Questions or comments?

Call toll free 1-877-274-8358

COMPARE TO Colgate Cavity Protection*

• HELPS PREVENT CAVITIES
• GREAT MINT TASTE

DISTRIBUTED BY LIDL US, LLC
3500 S. CLARK STREET,
ARLINGTON, VA 22202
PRODUCT OF INDIA
1-844-344-5071
WWW.LIDL.COM

*THIS PRODUCT IS NOT MANUFACTURED OR DISTRIBUTED BY THE COLGATE-PALMOLIVE COMPANY, OWNER OF THE REGISTERED TRADEMARK COLGATE®.

Lidl Love It!
GUARANTEE
√money refunded
√item replaced